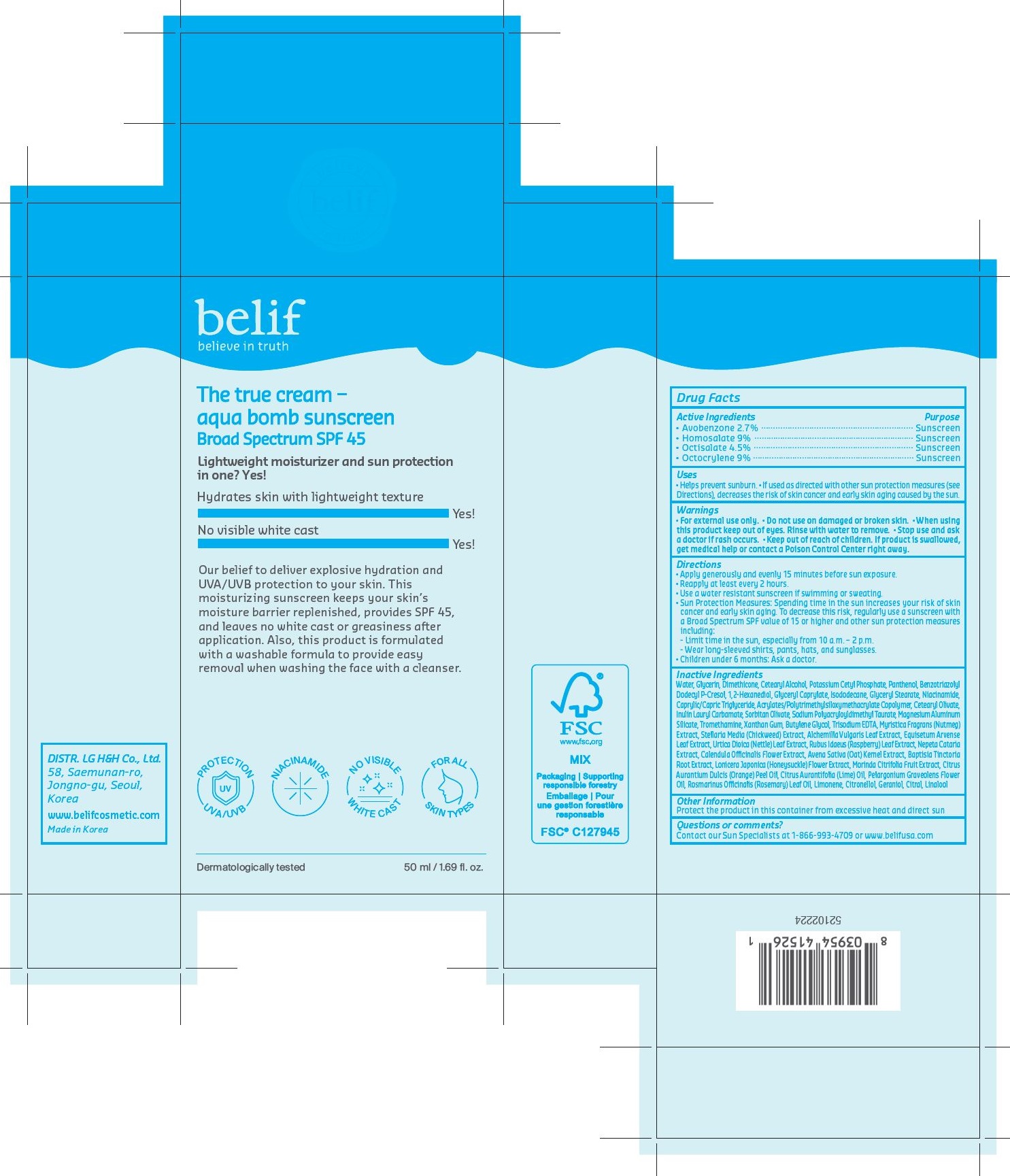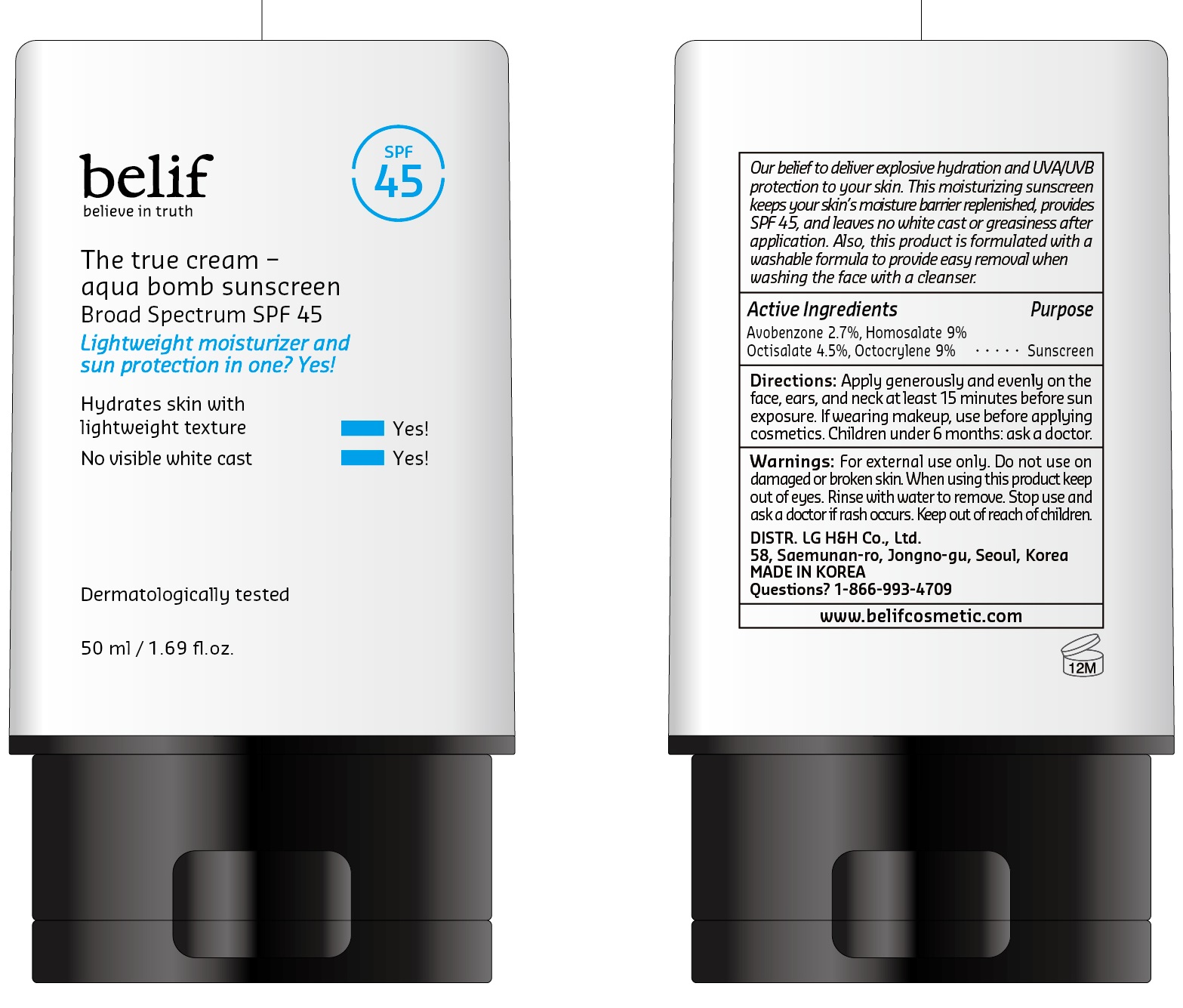 DRUG LABEL: belif The true cream aqua bomb sunscreen Broad Spectrum SPF 45
NDC: 53208-721 | Form: CREAM
Manufacturer: LG H&H Co.,Ltd.
Category: otc | Type: HUMAN OTC DRUG LABEL
Date: 20240219

ACTIVE INGREDIENTS: OCTISALATE 4.5 g/50 mL; HOMOSALATE 9 g/50 mL; AVOBENZONE 2.7 g/50 mL; OCTOCRYLENE 9 g/50 mL
INACTIVE INGREDIENTS: WATER

belif The true cream aqua bomb sunscreen Broad Spectrum SPF 45 (50ml)

ACTIVE INGREDIENTS

Avobenzone 2.7%
Homosalate 9%
Octisalate 4.5%
Octocrylene 9%

PURPOSE

Sunscreen

USES

- Helps prevent sunburn.
- If used as directed with other sun protection measures (see Directions), decreases the risk of skin cancer and early skin aging caused by the sun.

WARNINGS

- For external use only.

- Do not use on damaged or broken skin.

- When using this product keep out of eyes. Rinse with water to remove.

- Stop use and ask doctor if rash occurs.

- Keep out of reach of children. If product is swallowed, get medical help or contact a Poison Control Center right away.

DIRECTIONS

- Apply generously and evenly 15 minutes before sun exposure.
- Reapply at least every 2 hours.
- Use a water resistant sunscreen if swimming or sweating.
- Sun Protection Measures. Spending time in the sun increases your risk of skin cancer and early skin aging. To decrease this risk, regularly use a sunscreen with a Broad Spectrum SPF value of 15 or higher and other sun protection measures including:

- Limit time in the sun, especially from 10 a.m. - 2 p.m.

- Wear long-sleeved shirts, pants, hats, and sunglasses.

- Children under 6 months: Ask a doctor.

INACTIVE INGREDIENTS

Water, Glycerin,

OTHER INFORMATION

Protect the product in this container from excessive heat and direct sun

QUESTIONS OR COMMENTS?

Contact our Sun Specialist at 1-866-993-4709 or www.belifusa.com

DISTR. LG H&H Co., Ltd.
58, Saemunan-ro,
Jongno-gu, Seoul,
Korea

www.belifcosmetic.com

Made in Korea

PRINCIPAL DISPLAY PANEL

belif
believe in truth

The true cream -
aqua bomb sunscreen
Broad Spectrum SPF 45
Lightweight moisturizer and sun protection
in one? Yes!

Hydrates skin with lightweight texture
------------------------------------------------------------ Yes

No visible white cast
------------------------------------------------------------ Yes

Our belief to deliver explosive hydration and
UVA/UVB protection to your skin. This
moisturizing sunscreeen keeps your skin's
moisture barrier replenished, provides SPF 45,
and leaves no white cast or greasiness after
application. Also, this product is formulated
with a washable formula to provide easy
removal when washing the face with a cleanser.

(PROTECTION UVA/UVB)

(NIACINAMIDE)

(NO VISIBLE WHITE CAST)

(FOR ALL SKIN TYPES)

Dermatologically tested

50 ml / 1.69 fl. oz.